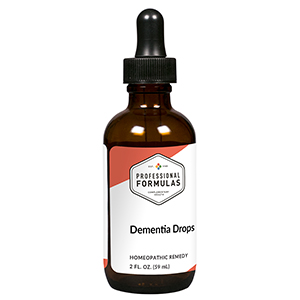 DRUG LABEL: Dementia Drops
NDC: 63083-2117 | Form: LIQUID
Manufacturer: Professional Complementary Health Formulas
Category: homeopathic | Type: HUMAN OTC DRUG LABEL
Date: 20190815

ACTIVE INGREDIENTS: TURNERA DIFFUSA LEAF 1 [hp_X]/59 mL; CELERY SEED 3 [hp_X]/59 mL; ANHYDROUS DIBASIC CALCIUM PHOSPHATE 3 [hp_X]/59 mL; HYOSCYAMUS NIGER 4 [hp_X]/59 mL; BARIUM CARBONATE 6 [hp_X]/59 mL; OYSTER SHELL CALCIUM CARBONATE, CRUDE 6 [hp_X]/59 mL; PHOSPHORIC ACID 6 [hp_X]/59 mL; ZINC 6 [hp_X]/59 mL; GOLD MONOIODIDE 8 [hp_X]/59 mL; PICRIC ACID 10 [hp_X]/59 mL; PHOSPHORUS 12 [hp_X]/59 mL; LILIUM LANCIFOLIUM WHOLE FLOWERING 12 [hp_X]/59 mL; SULFUR 30 [hp_X]/59 mL
INACTIVE INGREDIENTS: ALCOHOL; WATER

C117

ACTIVE INGREDIENTS

Turnera diffusa 1X
Apium graveolens 3X
Calcarea phosphorica 3X
Hyoscyamus niger 4X
Baryta carbonica 6X
Calcarea carbonica 6X
Phosphoricum acidum 6X
Zincum metallicum 6X
Aurum iodatum 8X
Picricum acidum 10X
Phosphorus 12X
Lilium tigrinum 12X, 30X
Sulphur 30X

QUESTIONS

Professional Formulas

PO Box 2034 Lake Oswego, OR 97035

INDICATIONS

For temporary relief of irritability, anxiousness, mood swings, forgetfulness, or confusion.*

PURPOSE

*Claims based on traditional homeopathic practice, not accepted medical evidence. Not FDA evaluated.

WARNINGS

Consult a doctor if condition worsens or if symptoms persist. Keep out of the reach of children. In case of overdose, get medical help or contact a poison control center right away. If pregnant or breastfeeding, ask a healthcare professional before use.

Keep out of the reach of children.

PREGNANCY OR BREAST FEEDING

If pregnant or breastfeeding, ask a healthcare professional before use.

DIRECTIONS

Place drops under tongue 30 minutes before/after meals. Adults and children 12 years and over: Take 10 drops up to 3 times per day. Consult a physician for use in children under 12 years of age.

OTHER INFORMATION

Tamper resistant. If seal is broken, do not use. After opening, close container tightly and store at room temperature away from heat.

INACTIVE INGREDIENTS

20% ethanol, purified water.

LABEL

Est 1985

Professional Formulas

Complementary Health

Dementia Drops

Homeopathic Remedy

2 FL. OZ. (59 mL)